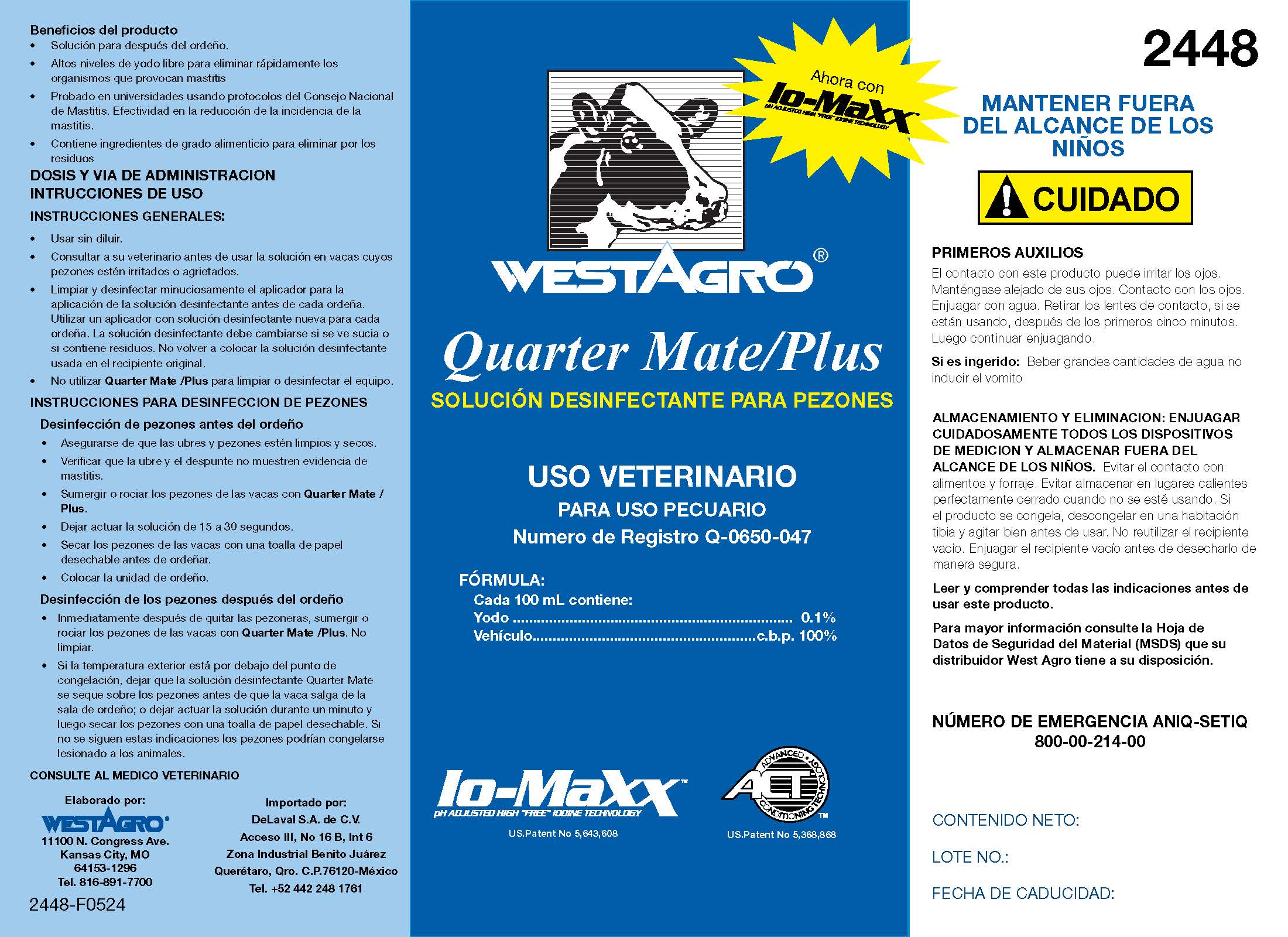 DRUG LABEL: Quarter Mate
NDC: 33392-448 | Form: SOLUTION
Manufacturer: WestAgro, Inc.
Category: animal | Type: OTC ANIMAL DRUG LABEL
Date: 20240511

ACTIVE INGREDIENTS: Iodine 0.1 kg/100 kg
INACTIVE INGREDIENTS: FD&C BLUE NO. 1; SODIUM HYDROXIDE; ANHYDROUS CITRIC ACID; POLOXAMER 335; GLYCERIN; XANTHAN GUM; POLOXAMER 403; water; SODIUM CHLORIDE; FD&C RED NO. 40; FD&C YELLOW NO. 5; SODIUM IODIDE; DOCUSATE SODIUM; SODIUM IODATE

WESTAGRO QUARTER MATE/PLUS

SOLUCIÓN DESINFECTANTE PARA PEZONES

USO VETERINATIO

PARA USO PECUARIO

Numero de Registro Q-0650-047

ACTIVE INGREDIENT

FÓRMULA:

Cada 100 mL contiene:

Yodo ...................................... 0.1%

Vehculo .........................c.b.p. 100%

ACT
ADVANCED CONDITIONING TECHNOLOGY

Io-MaXX
pH ADJUSTED HIGH "FREE" IODINE TECHNOLOGY

Manufactured by:
WESTAGRO
11100 N. Congress Ave.

Kansas City, MO
Tel. 816-891-7700

Importado por:

DeLaval S.A. de C.V.

Acceso lll, No 16 B, Int 6

Zona Industrial Benito Juárez

Querétaro, Qro. C.P.76120-México

Tel. +52 442 248 1761

PRODUCT BENEFITS

- Pre-dip, post-dip, the only dip you need.
- Elevated free iodine for fast kill of mastitis causing organisms.
- University tested using National Mastitis Council protocols. Proven effective in reducing the incidence of mastitis.
- Contains food grade ingredients to eliminate residue concerns.

INDICATIONS AND USAGE

DIRECTIONS FOR USE:
GENERAL INSTRUCTIONS

- Use at full strength (Do not dilute).
- Consult your veterinarian before using teat dip on a cow with sore or chapped teats.
- Thoroughly clean and sanitize teat dip cup before each milking. Use fresh teat dip for each milking. Dip solution should be changed if it becomes visibly dirty, or if sediment is introduced. Do not pour used teat dip back into original container.
- Do not use Quarter Mate teat dip for cleaning or sanitizing equipment.

PRE-DIPPING

- Make sure udder and teats are clean and dry.
- Check foremilk and udder for mastitis.
- Dip or spray cow's teats with Quarter Mate teat dip.
- Allow 15 to 30 seconds contact time.
- Dry cow's teats with a single service paper towel before milking.
- Attach milker unit.

POST DIPPING

- Immediately after removing inflations, dip or spray cow's teats with Quarter Mate teat dip. Do not wipe.
- If outside temperature is below freezing, allow Quarter Mate teat dip to air-dry on cow's teats before cow leaves the parlor; or allow teat dip to remain on cow's teats for one minute, then dry teats with single service paper towel.

Failure to follow these directions may result in frozen teats and injured animals.

Color added to indicate contact with the animal.

KEEP OUT OF REACH OF CHILDREN

MANTENER FUERA DEL ALCANCE DE LOS NINOS

! CUIDADO

FIRST AID

Contact with product can cause irritation to eyes. Keep out of eyes.
Eye Contact: Flush with water. Remove contact lenses, if present, after the first five minutes. Then continue flushing.
If Swallowed: Drink large quantities of water and induce vomiting.

STORAGE AND DISPOSAL:

THOROUGHLY RINSE ALL MEASURING DEVICES AND STORE OUT OF REACH OF CHILDREN. Avoid contact with food or feed. Avoid storing near heat or open flame. Keep container tightly closed when not in use. If product has frozen, thaw in a warm room and shake well before use. Do not reuse empty container. Rinse empty container before disposing in a safe manner.

Read and understand all directions before using this product. For additional information refer to the Material Safety Data Sheet (MSDS) available from your West Agro dealer.

CHEMTREC EMERGENCY NO. 800-00-214-00

NET
CONTENTS:

LOT NO:

EXPIRATION DATE:

PACKAGE LABEL

Add image transcription here...